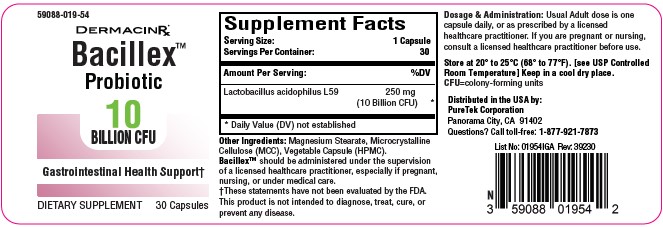 DRUG LABEL: Bacillex
NDC: 59088-019 | Form: CAPSULE
Manufacturer: PureTek Corporation
Category: other | Type: DIETARY SUPPLEMENT
Date: 20250626

ACTIVE INGREDIENTS: LACTOBACILLUS ACIDOPHILUS 10000000000 [CFU]/1 1

Bacillex™

STATEMENT OF IDENTITY

Bacillex™

Serving Size: 1 Capsule

Servings Per Container: 30

Amount Per Serving:

Proprietary Blend: 10 billion CFU (Colony Forming Units)
Lactobacillus acidophilus L59: Identified as the specific strain included in the blend

Other Ingredients: Magnesium Stearate, Microcrystalline Cellulose (MCC), Vegetable Capsule (HPMC).

Dosage & Administrationz:

Usual Adult dose is one capsule daily, or as prescribed by a licensed healthcare practitioner. If you are pregnant or nursing, consult a licensed healthcare practitioner before use.

SAFE HANDLING

This product is contraindicated in patients with a known hypersensitivity to any of the ingredients.

Bacillex™ should be administered under the supervision of a licensed healthcare practitioner, especially if pregnant, nursing, or under medical care.

†These statements have not been evaluated by the FDA. This product is not intended to diagnose, treat, cure, or prevent any disease.

KEEP THIS AND ALL MEDICATIONS OUT OF THE REACH OF CHILDREN. Do not use if bottle seal is broken.

STORAGE

Store at 20° to 25°C (68° to 77°F). [see USP Controlled Room Temperature] Keep in a cool dry place.

HOW SUPPLIED HEALTH CLAIM

Bacillex™, Probiotic

Dietary Supplement

NHRIC: 59088-019-54 *

Bottles contain 30 Capsules

Distributed in the USA by:
PureTek Corporation
Panorama City, CA 91402
Questions? Call toll-free:
1-877-921-7873

*Does not represent these product codes to be National Drug Codes (NDC). Product codes are formatted according to standard industry practice, to meet the formatting requirement by pedigree reporting and supply-chain control including pharmacies.

The most appropriate way to ensure pedigree reporting consistent with these regulatory guidelines and safety monitoring is to dispense this product by prescription. This is not an Orange Book product. This product may be administered only under a physician’s supervision and all prescriptions using this product shall be pursuant to state statutes as applicable. The ingredients, indication or claims of this product are not to be construed to be drug claims.